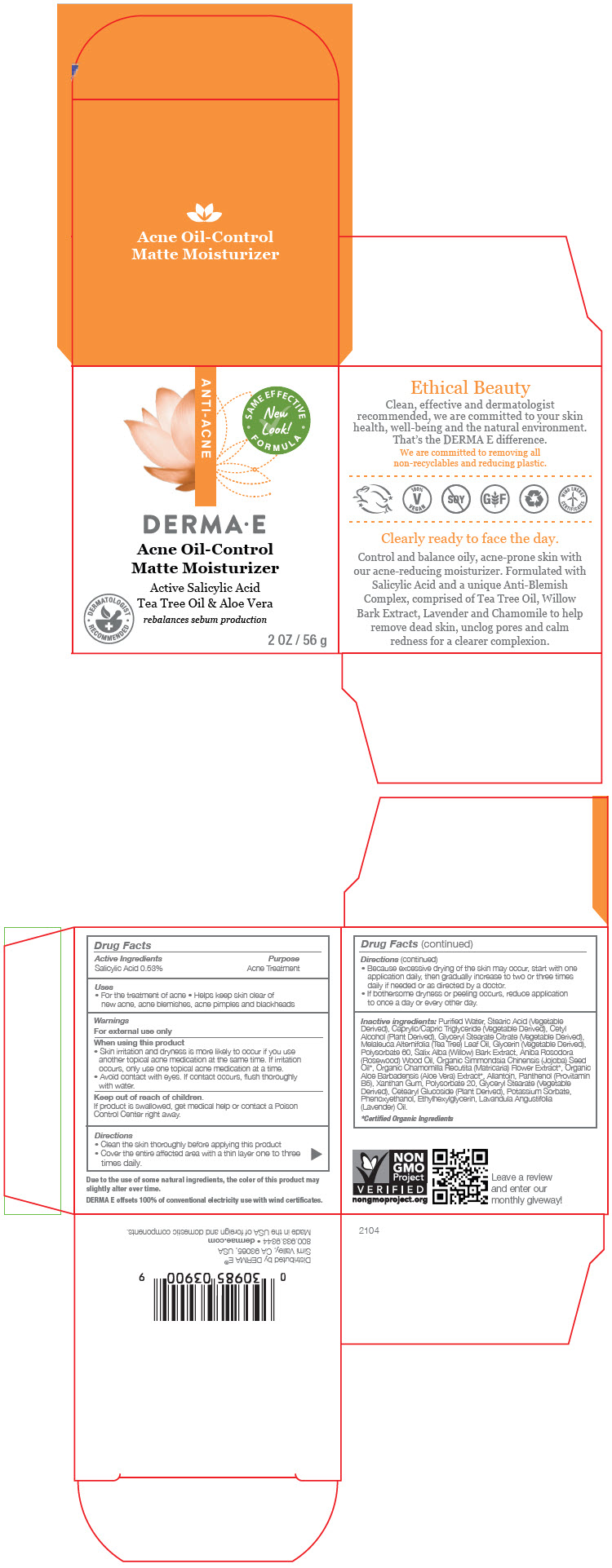 DRUG LABEL: Derma E Acne  Matte Moisturizer
NDC: 54108-3900 | Form: LOTION
Manufacturer: derma e
Category: otc | Type: HUMAN OTC DRUG LABEL
Date: 20240531

ACTIVE INGREDIENTS: SALICYLIC ACID 5.3 mg/1 g
INACTIVE INGREDIENTS: WATER; STEARIC ACID; MEDIUM-CHAIN TRIGLYCERIDES; CETYL ALCOHOL; GLYCERYL STEARATE CITRATE; TEA TREE OIL; GLYCERIN; POLYSORBATE 60; SALIX ALBA BARK; ROSEWOOD OIL; JOJOBA OIL; CHAMOMILE; ALOE VERA FLOWER; ALLANTOIN; PANTHENOL; XANTHAN GUM; POLYSORBATE 20; GLYCERYL STEARATE SE; CETEARYL GLUCOSIDE; POTASSIUM SORBATE; PHENOXYETHANOL; ETHYLHEXYLGLYCERIN; LAVENDER OIL

Derma E Acne Matte Moisturizer

Drug Facts

Active Ingredients

Salicylic Acid 0.53%

Purpose

Acne Treatment

Uses

- For the treatment of acne
- Helps keep skin clear of new acne, acne blemishes, acne pimples and blackheads

Warnings

For external use only

When using this product

- Skin irritation and dryness is more likely to occur if you use another topical acne medication at the same time. If irritation occurs, only use one topical acne medication at a time.
- Avoid contact with eyes. If contact occurs, flush thoroughly with water.

Keep out of reach of children.

If product is swallowed, get medical help or contact a Poison Control Center right away.

Directions

- Clean the skin thoroughly before applying this product
- Cover the entire affected area with a thin layer one to three times daily.
- Because excessive drying of the skin may occur, start with one application daily, then gradually increase to two or three times daily if needed or as directed by a doctor.
- If bothersome dryness or peeling occurs, reduce application to once a day or every other day.

Inactive ingredients

Purified Water, Stearic Acid (Vegetable Derived), Caprylic/Capric Triglyceride (Vegetable Derived), Cetyl Alcohol (Plant Derived), Glyceryl Stearate Citrate (Vegetable Derived), Melaleuca Alternifolia (Tea Tree) Leaf Oil, Glycerin (Vegetable Derived), Polysorbate 60, Salix Alba (Willow) Bark Extract, Aniba Rosodora (Rosewood) Wood Oil, Organic Simmondsia Chinensis (Jojoba) Seed Oil*, Organic Chamomilla Recutita (Matricaria) Flower Extract [Certified Organic Ingredients] , Organic Aloe Barbadensis (Aloe Vera) Extract*, Allantoin, Panthenol (Provitamin B5), Xanthan Gum, Polysorbate 20, Glyceryl Stearate (Vegetable Derived), Cetearyl Glucoside (Plant Derived), Potassium Sorbate, Phenoxyethanol, Ethylhexylglycerin, Lavandula Angustifolia (Lavender) Oil.

Distributed by DERMA E®
Simi Valley, CA 93065, USA

PRINCIPAL DISPLAY PANEL - 56 g Tube Box

ANTI-ACNE

• SAME EFFECTIVE
FORMULA •
New
Look!

DERMA•E
Acne Oil-Control
Matte Moisturizer

Active Salicylic Acid
Tea Tree Oil & Aloe Vera
rebalances sebum production

• DERMATOLOGIST
RECOMMENDED •

2 OZ / 56 g